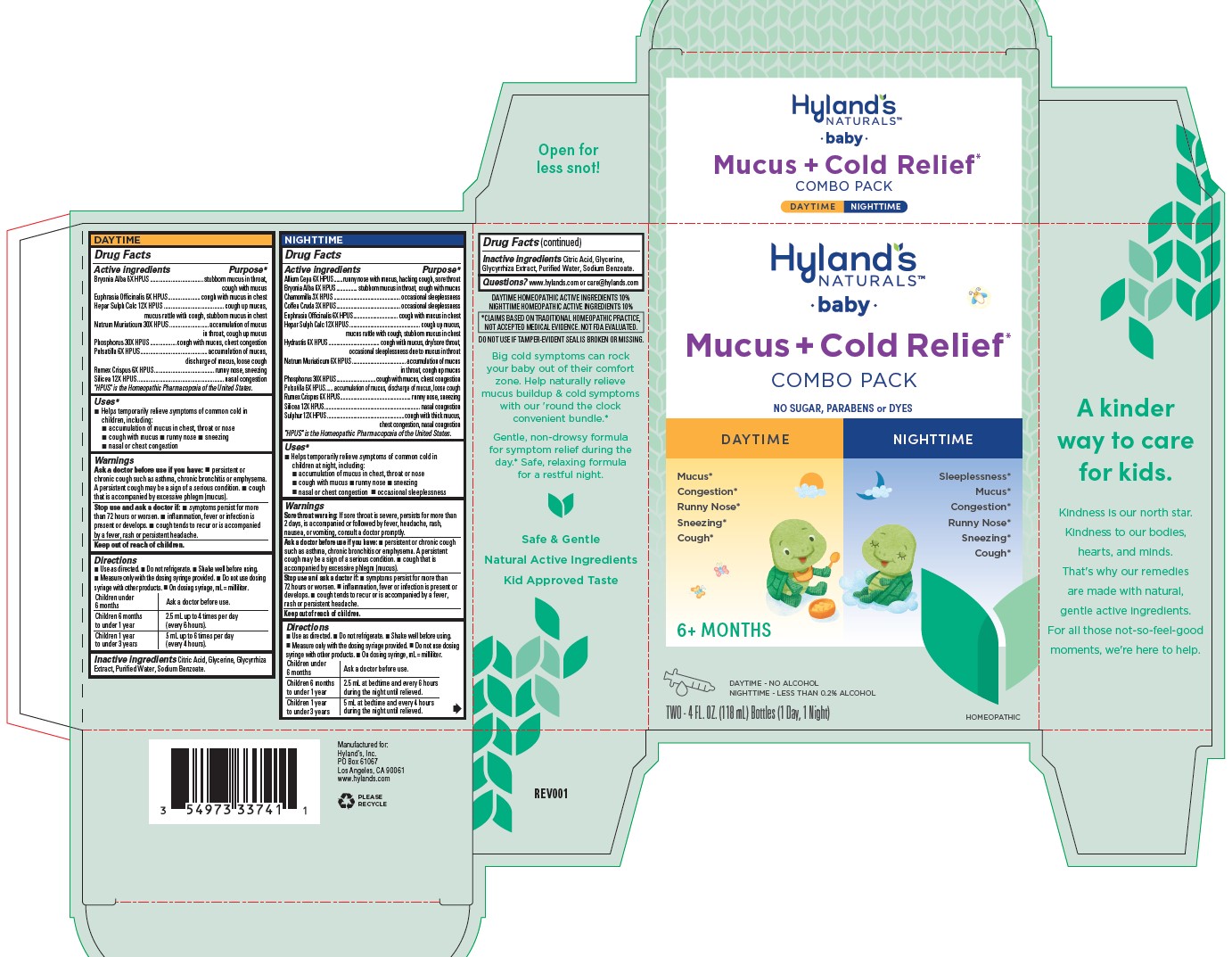 DRUG LABEL: BABY MUCUS PLUS COLD RELIEF DAYTIME AND NIGHTTIME
NDC: 54973-3374 | Form: KIT | Route: ORAL
Manufacturer: Hyland's Inc.
Category: homeopathic | Type: HUMAN OTC DRUG LABEL
Date: 20230823

ACTIVE INGREDIENTS: ANEMONE PULSATILLA 6 [hp_X]/1 mL; RUMEX CRISPUS ROOT 6 [hp_X]/1 mL; SILICON DIOXIDE 12 [hp_X]/1 mL; BRYONIA ALBA ROOT 6 [hp_X]/1 mL; EUPHRASIA STRICTA 6 [hp_X]/1 mL; CALCIUM SULFIDE 12 [hp_X]/1 mL; SODIUM CHLORIDE 30 [hp_X]/1 mL; PHOSPHORUS 30 [hp_X]/1 mL; CALCIUM SULFIDE 12 [hp_X]/1 mL; ONION 6 [hp_X]/1 mL; PHOSPHORUS 30 [hp_X]/1 mL; BRYONIA ALBA ROOT 6 [hp_X]/1 mL; MATRICARIA CHAMOMILLA 3 [hp_X]/1 mL; SULFUR 12 [hp_X]/1 mL; RUMEX CRISPUS ROOT 6 [hp_X]/1 mL; ARABICA COFFEE BEAN 3 [hp_X]/1 mL; ANEMONE PULSATILLA 6 [hp_X]/1 mL; SILICON DIOXIDE 12 [hp_X]/1 mL; EUPHRASIA STRICTA 6 [hp_X]/1 mL; SODIUM CHLORIDE 6 [hp_X]/1 mL; GOLDENSEAL 6 [hp_X]/1 mL
INACTIVE INGREDIENTS: SODIUM BENZOATE; GLYCERIN; LICORICE; CITRIC ACID MONOHYDRATE; WATER; GLYCYRRHIZA GLABRA; SODIUM BENZOATE; WATER; CITRIC ACID MONOHYDRATE; GLYCERIN

Hyland's Naturals Baby Mucus + Cold Relief Combo Pack Daytime & Nighttime

DAYTIME

Drug Facts

Active ingredients | Purpose*
Bryonia Alba 6X HPUS | stubborn mucus in throat, cough with mucus
Euphrasia Officinalis 6X HPUS | cough with mucus in chest
Hepar Sulph Calc 12X HPUS | cough up mucus, mucus rattle with cough, stubborn mucus in chest
Natrum Muriaticum 30X HPUS | accumulation of mucus in throat, cough up mucus
Phosphorus 30X HPUS | cough with mucus, chest congestion
Pulsatilla 6X HPUS | accumulation of mucus, discharge of mucus, loose cough
Rumex Crispus 6X HPUS | runny nose, sneezing
Silicea 12X HPUS | nasal congestion

HPUS" is the Homeopathic Pharmacopoeia of the United States.

Uses*

■ Helps temporarily relieve symptoms of common cold in children, including:

■ accumulation of mucus in chest, throat or nose
■ cough with mucus ■ runny nose ■ sneezing
■ nasal or chest congestion

Warnings

Ask a doctor before use if you have

■ persistent or chronic cough such as asthma, chronic bronchitis or emphysema. A persistent cough may be a sign of a serious condition. ■ cough that is accompanied by excessive phlegm (mucus).

Stop use and ask a doctor if

■ symptoms persist for more than 72 hours or worsen. ■ inflammation, fever or infection is present or develops. ■ cough tends to recur or is accompanied by a fever, rash or persistent headache.

Directions

■ Use as directed. ■ Do not refrigerate. ■ Shake well before using.
■ Measure only with the dosing syringe provided. ■ Do not use dosing
syringe with other products. ■ On dosing syringe, mL = milliliter.

Children under 6 months | Ask a doctor before use.
Children 6 months to under 1 year | 2.5 mL up to 4 times per day (every 6 hours).
Children 1 year to under 3 years | 5 mL up to 6 times per day (every 4 hours).

Inactive ingredients

Citric Acid, Glycerine, Glycyrrhiza Extract, Purified Water, Sodium Benzoate.

NIGHTTIME

Drug Facts

Active ingredients | Purpose*
Allium Cepa 6X HPUS | runny nose with mucus, hacking cough, sore throat
Bryonia Alba 6X HPUS | stubborn mucus in throat, cough with mucus
Chamomilla 3X HPUS | occasional sleeplessness
Coffea Cruda 3X HPUS | occasional sleeplessness
Euphrasia Offcinalis 6X HPUS | cough with mucus in chest
Hepar Sulph Calc 12X HPUS | cough up mucus, mucus rattle with cough, stubborn mucus in chest
Hydrastis 6X HPUS | cough with mucus, dry/sore throat, occasional sleeplessness due to mucus in throat
Natrum Muriaticum 6X HPUS | accumulation of mucus in throat, cough up mucus
Phosphorus 30X HPUS | cough with mucus, chest congestion
Pulsatilla 6X HPUS | accumulation of mucus, discharge of mucus, loose cough
Rumex Crispus 6X HPUS | runny nose, sneezing
Silicea 12X HPUS | nasal congestion
Sulphur 12X HPUS | cough with thick mucus, chest congestion, nasal congestion

"HPUS" is the Homeopathic Pharmacopoeia of the United States.

Uses*

■ Helps temporarily relieve symptoms of common cold in children at night, including:
■ accumulation of mucus in chest, throat or nose
■ cough with mucus ■ runny nose ■ sneezing
■ nasal or chest congestion ■ occasional sleeplessness

Warnings

Sore throat warning

If sore throat is severe, persists for more than 2 days, is accompanied or followed by fever, headache, rash, nausea, or vomiting, consult a doctor promptly.

Ask a doctor before use if you have

■ persistent or chronic cough such as asthma, chronic bronchitis or emphysema. A persistent cough may be a sign of a serious condition. ■ cough that is accompanied by excessive phlegm (mucus).

Stop use and ask a doctor if

■ symptoms persist for more than 72 hours or worsen.

■ inflammation, fever or infection is present or develops.

■ cough tends to recur or is accompanied by a fever, rash or persistent headache.

Directions

■ Use as directed. ■ Do not refrigerate. ■ Shake well before using. ■ Measure only with the dosing syringe provided. ■ Do not use dosing syringe with other products. ■ On dosing syringe, mL = milliliter.

Children under 6 months | Ask a doctor before use.
Children 6 months to under 1 year | 2.5 mL at bedtime and every 6 hours during the night until relieved.
Children 1 year to under 3 years | 5 mL at bedtime and every 4 hours during the night until relieved.

Drug Facts (continued)

Inactive ingredients

Citric Acid, Glycerine,Glycyrrhiza Extract, Purified Water, Sodium Benzoate.

Questions?

www.hylands.com or care@hylands.com

PURPOSE

Helps temporarily relieve symptoms of common cold in children at night, including: accumulation of mucus in chest, throat or nose,
cough with mucus, runny nose, sneezing, nasal or chest congestion, occasional sleeplessness.

Indications and Usage

Added asterisk (*) to Uses for Daytime and Nighttime

Principal Display Panel

Hyland's

NATURALS™

•baby•

Mucus + Cold Relief*

COMBO PACK

NO SUGAR, PARABENS or DYES

DAYTIME

Mucus*

Congestion*

Runny Nose*

Sneezing*

Cough*

NIGHTTIME

Sleeplessness*

Mucus*

Congestion*

Runny Nose*

Sneezing*

Cough*

6+ MONTHS

DAYTIME - NO ALCOHOL

NIGHTTIME - LESS THAN 0.2% ALCOHOL

TWO - 4 FL. OZ. (118 mL) Bottles (1 Day, 1 Night)

HOMEOPATHIC